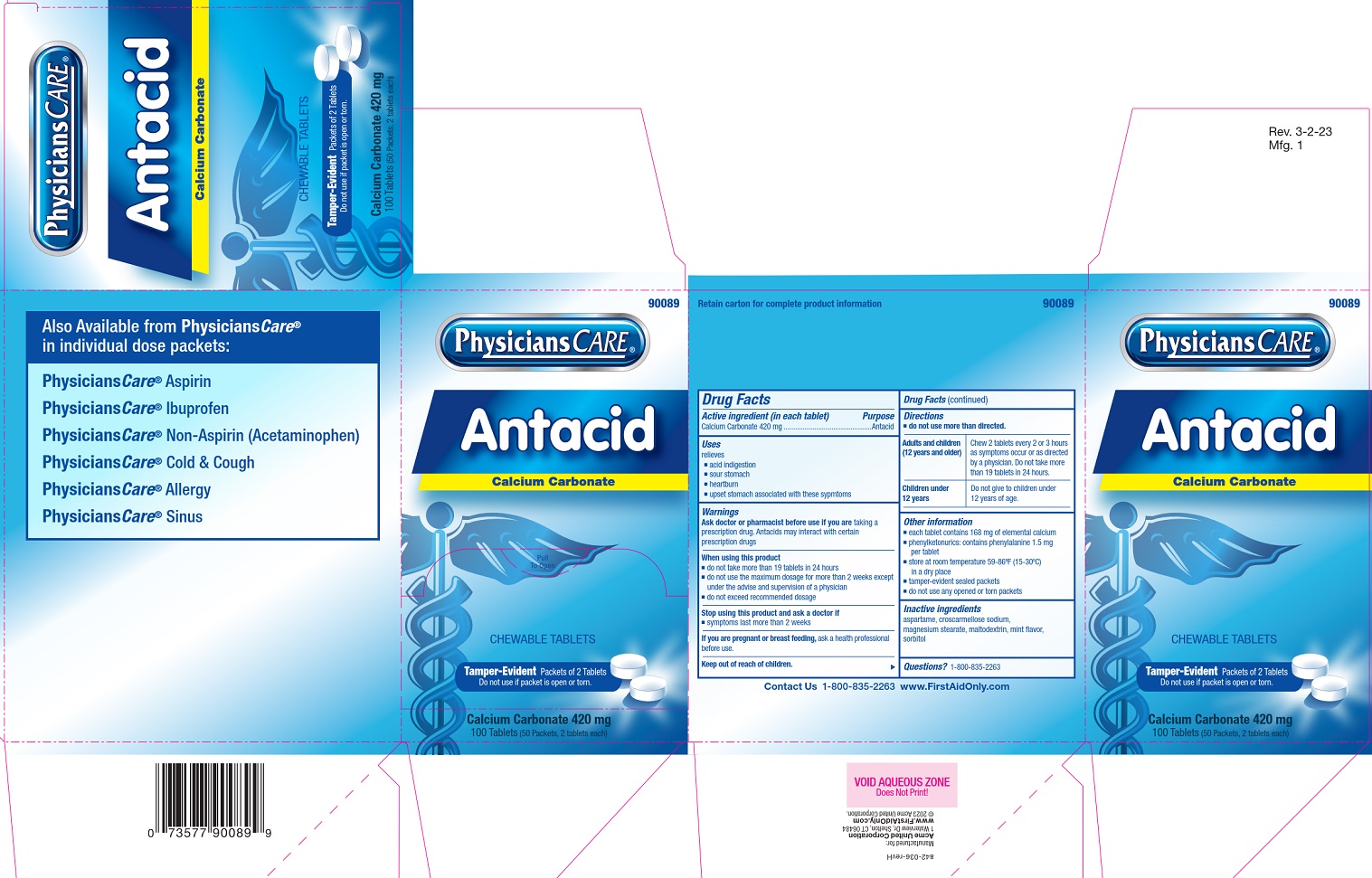 DRUG LABEL: PhysiciansCare Antacid
NDC: 0924-0086 | Form: TABLET, CHEWABLE
Manufacturer: Acme United Corporation
Category: otc | Type: HUMAN OTC DRUG LABEL
Date: 20250908

ACTIVE INGREDIENTS: CALCIUM CARBONATE 420 mg/1 1
INACTIVE INGREDIENTS: ASPARTAME; CROSCARMELLOSE SODIUM; MALTODEXTRIN; MAGNESIUM STEARATE; SORBITOL

PhysiciansCare Antacid

Drug Facts

Active Ingredient (in each tablet)

Calcium Carbonate 420 mg

Purpose

Antacid

Uses

relieves

■ acid indigestion

■ sour stomach

■ heartburn

■ upset stomach associated with these symptoms

Warnings

Ask a doctor or pharmacist before use if you are taking a prescription drug. Antacids may interact with certain prescription drugs.

When using this product

- do not take more than 19 tablets in 24 hours
- do not use the maximum dosage for more than 2 weeks except under the advice and supervision of a physician
- do not exceed recommended dosage

STOP USE

Stop using this product and ask a doctor if

- symptoms last more than 2 weeks

PREGNANCY OR BREAST FEEDING

If you are pregnant or breastfeeding, ask a health professional before use.

Keep out of the reach of children.

Directions

- do not use more than directed

Adults and children (12 years and older) Chew 2 tablets every 2 or 3 hours as symptoms occur or as directed by a physician. Do not take more than 19 tablets in 24 hours.

Children under 12 years:

Do not give to children under 12 years of age

Other information

- each tablet contains 168 mg of elemental calcium
- phenylketonurics: contains phenylalanine 1.5 mg per tablet
- store at room temperature 59-86F (15-30C) in a dry place
- tamper-evident sealed packets
- do not use any opened or torn packets

Inactive ingredients

aspartame, croscarmellose sodium, magnesium stearate, maltodextrin, mint flavor, sorbitol

Questions?1-800-835-2263

Physicians Care Antacid Label

90089

Physicians Care®

Antacid

Calcium Carbonate

Pull To Open

Chewable Tablets

Tamper-Evident Packets of 2 Tablets

Do not use if packet is open or torn.

Calcium Carbonate 420 mg

100 Tablest (50 Packets, 2 each)